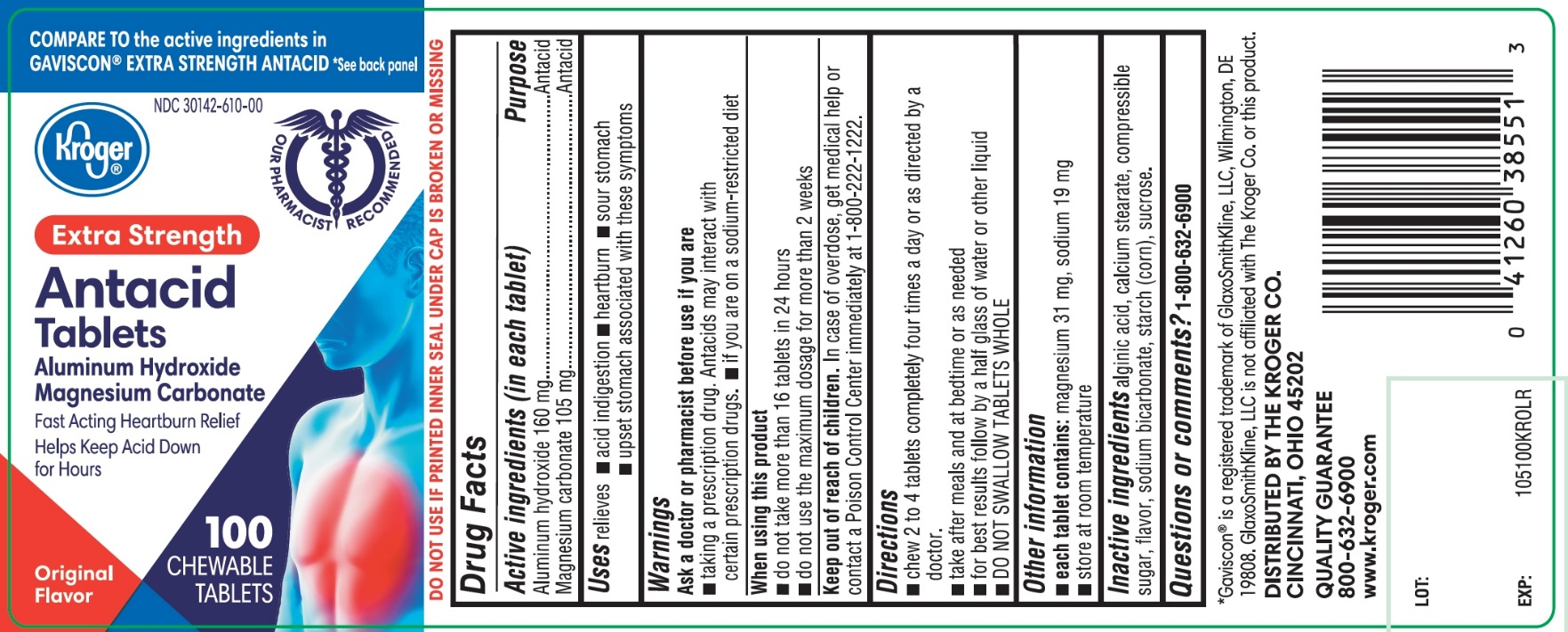 DRUG LABEL: Kroger Extra Strength
NDC: 30142-610 | Form: TABLET, CHEWABLE
Manufacturer: THE KROGER CO.,
Category: otc | Type: HUMAN OTC DRUG LABEL
Date: 20250801

ACTIVE INGREDIENTS: ALUMINUM HYDROXIDE 160 mg/1 1; MAGNESIUM CARBONATE 105 mg/1 1
INACTIVE INGREDIENTS: ALGINIC ACID; CALCIUM STEARATE; CORN SYRUP; SODIUM BICARBONATE; STARCH, CORN; SUCROSE

Kroger®Extra Strength 100 Chewable Tablets Original Flavor

Active ingredients (in each tablet)

Aluminum hydroxide 160 mg

Magnesium carbonate 105 mg

Purpose

Antacid

Antacid

Uses

relieves

- acid indigestion
- heartburn
- sour stomach
- upset stomach associated with these symptoms

Warnings

Ask a doctor or pharmacist before use if you are

- taking a prescription drug. Antacids may interact with certain prescription drugs
- If you are on a sodium-restricted diet

When using this product

- do not take more than 16 tablets in 24 hours
- do not use the maximum dosage for more than 2 weeks

Keep out of reach of children.

In case of overdose, get medical help or contact a Poison Control Center immediately at 1-800-222-1222.

Directions

- chew 2 to 4 tablets four times a day or as directed by a doctor
- take after meals and at bedtime or as needed
- for best results follow by a half glass of water or other liquid
- DO NOT SWALLOW TABLETS WHOLE

Other information

- each tablet contains: magnesium 31 mg, sodium 19 mg
- Store at room temperature.

Inactive ingredients

alginic acid, calcium stearate, compressible sugar, flavor, sodium bicarbonate, starch (corn), sucrose.

Questions or comments?

1-800-632-6900

Principal Display Panel

Kroger®

NDC 30142-610-00

COMPARE TO the active ingredients GAVISCON®EXTRA STRENGTH ANTACID

*See back panel

Antacid Tablets

EXTRA STRENGTH

Aluminum Hydroxide, 160 mg

Magnesium Carbonate, 105 mg

Fast Acting Heartburn Relief, Helps Keep Acid Down for Hours

- OUR PHARMACISTS RECOMMEND

100 CHEWABLE TABLETS

Original Flavor

DISTRIBUTED BY THE KROGER CO.

CINCINNATI, OHIO 45202

QUALITY GUARANTEE

800-632-6900 www.kroger.com

GLUTEN FREE

DO NOT USE IF PRINTED INNER SEAL UNDER CAP IS BROKEN OR MISSING

*GAVISCON®IS A REGISTERED TRADEMARK OF GLAXOSMITHKLINE LLC, WILMINGTON, DE 19808. GLAXOSMITHKLINE LLC IS NOT AFFLIATED WITH THE KROGER CO. OR THIS PRODUCT.